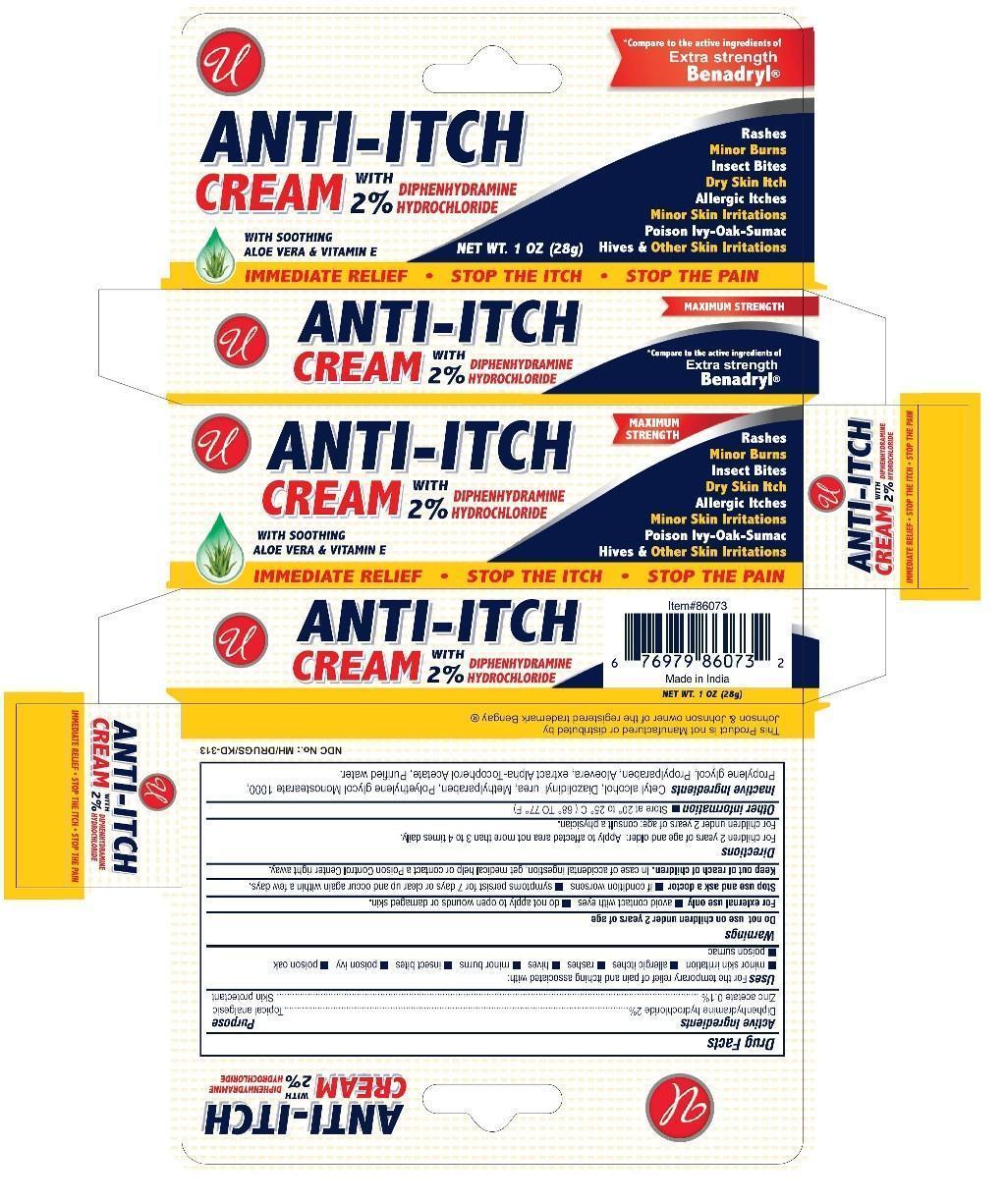 DRUG LABEL: Anti-Itch
NDC: 52000-023 | Form: CREAM
Manufacturer: Universal Distribution Center LLC
Category: otc | Type: HUMAN OTC DRUG LABEL
Date: 20241204

ACTIVE INGREDIENTS: DIPHENHYDRAMINE HYDROCHLORIDE 0.02 g/1 g; ZINC ACETATE 0.001 g/1 g
INACTIVE INGREDIENTS: ALOE VERA LEAF; .ALPHA.-TOCOPHEROL; WATER; CETYL ALCOHOL; DIAZOLIDINYL UREA; METHYLPARABEN; PEG-20 STEARATE; PROPYLENE GLYCOL; PROPYLPARABEN

Anti-Itch Cream

Active Ingredients

Diphenhydramine Hydrochloride 2%

Zinc Acetate 0.1%

Purpose

Topical Analgesic

Skin Protectant

Uses

For the temporary relief of pain and itching associated with:

- minor skin irritation
- allergic itches
- rashes
- hives
- minor burns
- insect bites
- poison ivy
- poison oak
- poison sumac

Warnings

Do not use on children under 2 years of age.

For external use only

- avoid contact with eyes
- do not apply to open wound or damaged skin.

Stop use and ask a doctor

- if condition worsens
- symptoms persist for 7 days or clear up and occur again within a few days.

Keep out of reach of children.

In case of accidental ingestion, get medical help or contact a Poison Control Center right away.

Directions

- For children 2 years of age and older: Apply to affected area not more than 3 to 4 times daily.
- For children under 2 years of age: consult a physician.

Other information

- Store at 20ºC to 25ºC (68ºF to 77ºF).

Inactive ingredients

Cetyl Alcohol, Diazolidinly urea, Methylparaben, Polyethylene Glycol Monostearate 1000, Propylene Gylcol, Propylparaben, Aloevera extract, Alpha-Tocopherol Acetate, Purified Water.

PACKAGE LABEL

PRINCIPAL DISPLAY PANEL

Anti-Itch Cream

NET WT 1 OZ (28 g)